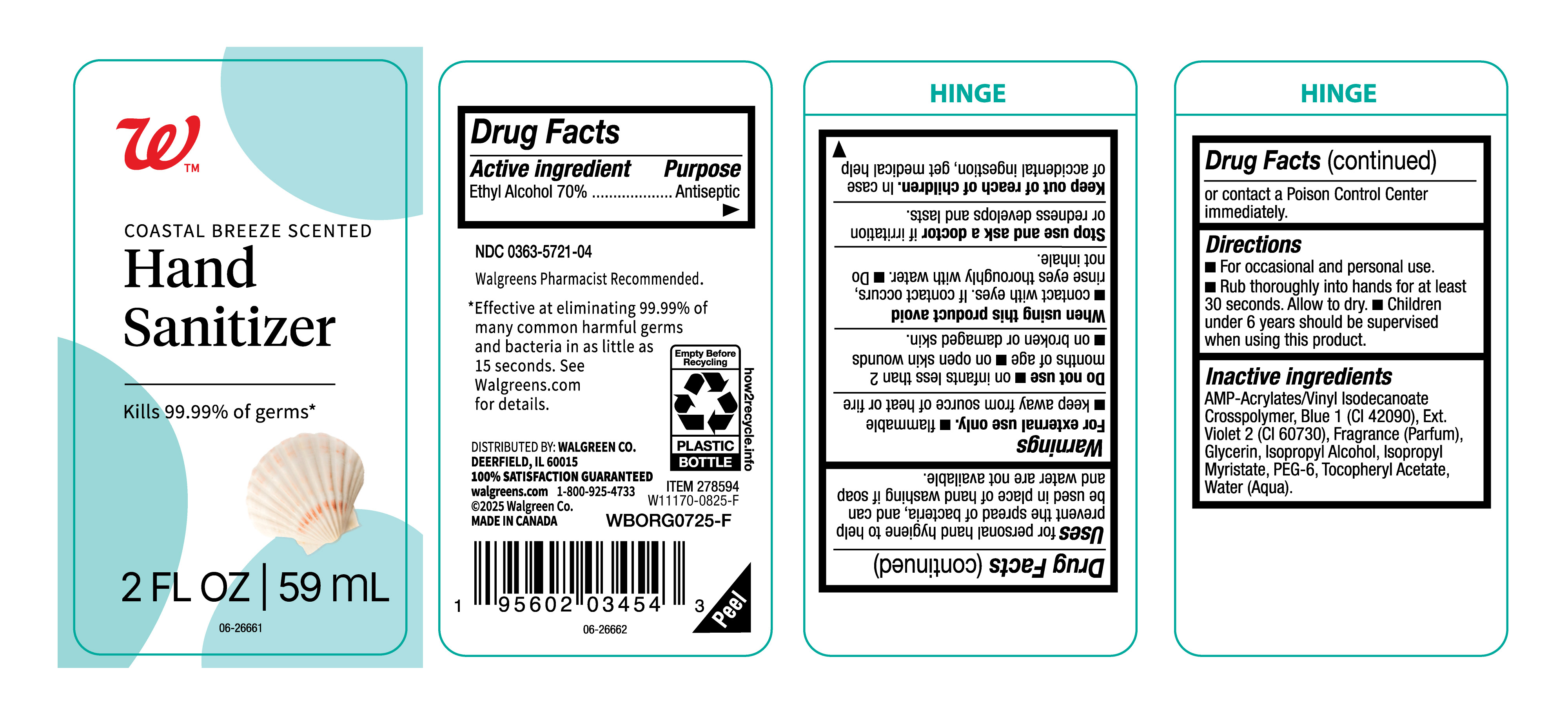 DRUG LABEL: Walgreens
NDC: 0363-5721 | Form: GEL
Manufacturer: walgreens
Category: otc | Type: HUMAN OTC DRUG LABEL
Date: 20250903

ACTIVE INGREDIENTS: ALCOHOL 700 mg/1 mL
INACTIVE INGREDIENTS: ISOPROPYL ALCOHOL; GLYCERIN; VIOLET 2; PEG-6; FRAGRANCE CLEAN ORC0600327; ISOPROPYL MYRISTATE; .ALPHA.-TOCOPHEROL ACETATE; BLUE 1; WATER; ACRYLATES/VINYL ISODECANOATE CROSSPOLYMER (10000 MPA.S NEUTRALIZED AT 0.5%)

NDC- 0363-5721-04, Walgreens Hand Sanitizer.

Active Ingredient

Ethyl Alcohol 70%

Purpose

Antiseptic

Uses

for personal hand hygiene to help prevent the spread of bacteria, and can be used in place of hand washing if soap andwater are not available.

For External use only

- flammable.
- Keep away from source of heat or fire.

Do not use

- on infants less than 2 months of age.
- On open skin wounds.
- On broken or damaged skin.

When using this product avoid

- Contact with eyes, if contact occurs, rinse eyes throughly with water.
- Do not inhale.

Stop use and ask a doctor

If irritation or redness develops and lasts.

Keep out of reach of children.

In case of accidental ingestion,get medical help or contact a Poison Control Center immediately.

Directions

- For Occassional and personal use.
- Rub thoroughly into hands for at least 30 seconds.Allow to dry.
- Children under 6 years should be supervised when using this product.

Inactive Ingredients

AMP-Acrylates/Vinyl Isodecanoate, Blue 1 (CI 42090), Ext.Violet 2 (CI 60730), Fragrance (Parfum), Glycerin, Isopropyl Alcohol, Isopropyl Myristate, PEG 6, Tocopheryl Acetate, Water (Aqua).